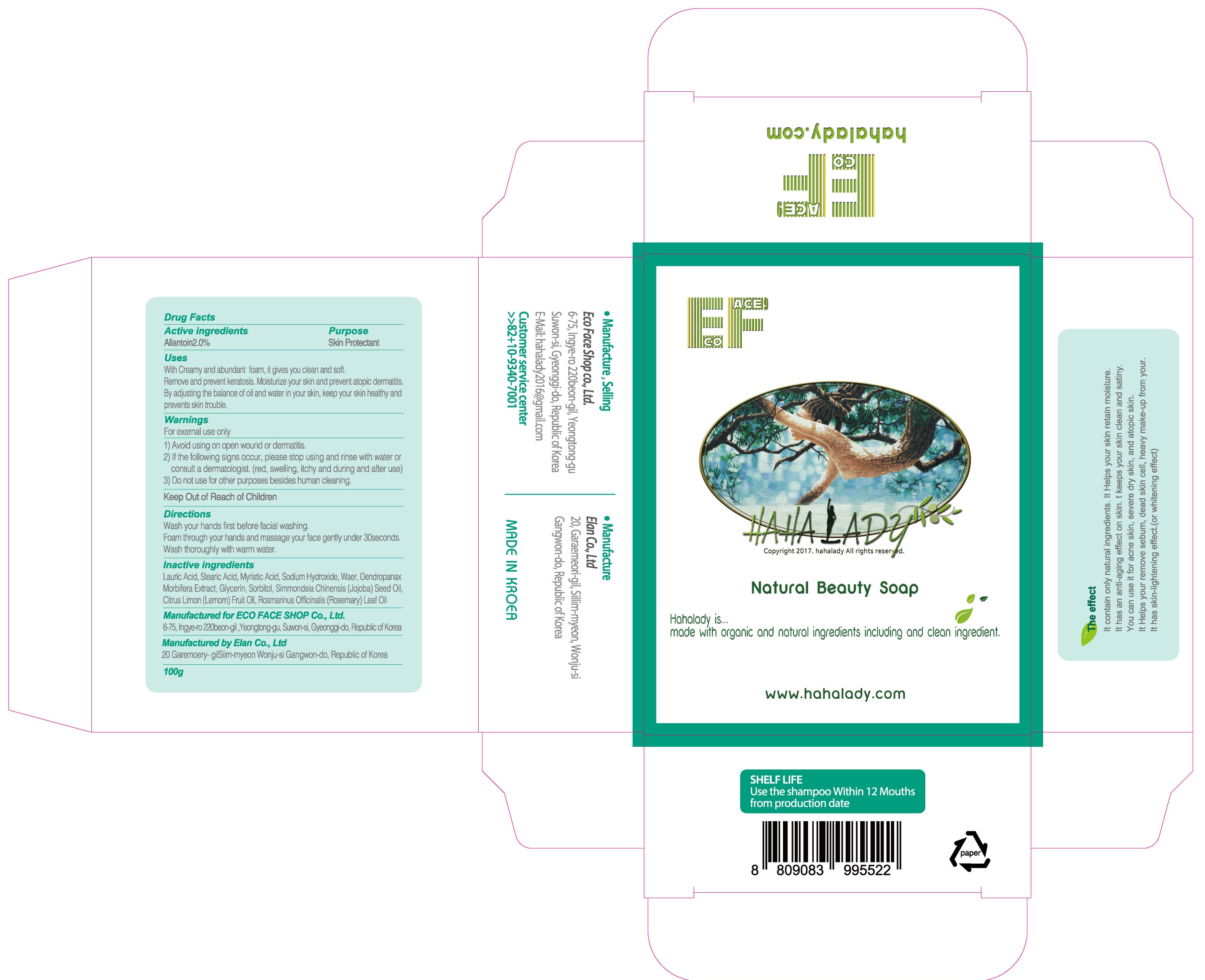 DRUG LABEL: HAHALADY
NDC: 71672-020 | Form: SOAP
Manufacturer: Eco Face Shop
Category: otc | Type: HUMAN OTC DRUG LABEL
Date: 20170915

ACTIVE INGREDIENTS: Allantoin 2.0 g/100 g
INACTIVE INGREDIENTS: Lauric Acid; Stearic Acid

ACTIVE INGREDIENT

Active ingredients: Allantoin 2.0%

INACTIVE INGREDIENT

Inactive ingredients: Lauric Acid,Stearic Acid, Myristic Acid,Sodium Hydroxide,Water,Dendropanax Morbifera Extract,Glycerin,Sorbitol,Simmondsia Chinensis (Jojoba) Seed Oil,,,Citrus Limon (Lemom) Fruit Oil,Rosmarinus Officinalis (Rosemary) Leaf Oil,Citrus Limon (Lemom) Fruit Oil,Rosmarinus Officinalis (Rosemary) Leaf Oil

PURPOSE

Purpose: Skin Protectant

WARNINGS

Warnings: For external use only 1)Avoid using on open wound or dermatitis . 2)If the following signs occur ,please stop using and rinse with water or consult a dermatologist .(red, swelling,itchy and during and after use) 3)Do not use for other purposes besides human cleaning.

KEEP OUT OF REACH OF CHILDREN

Uses

Uses: With Creamy and abundant foam, it gives you clean and soft. Remove and prevent keratosis.Moisturize your skin and prevent atopic dermatitis.By adjusting the balance of oil and water in your skin,keep your skin healthy.and prevents skin trouble..

Directions

Directions: Wash your hands first before facial washing. Foam through your hands and massage your face gently under 30seconds. Wash thoroughly with warm water.